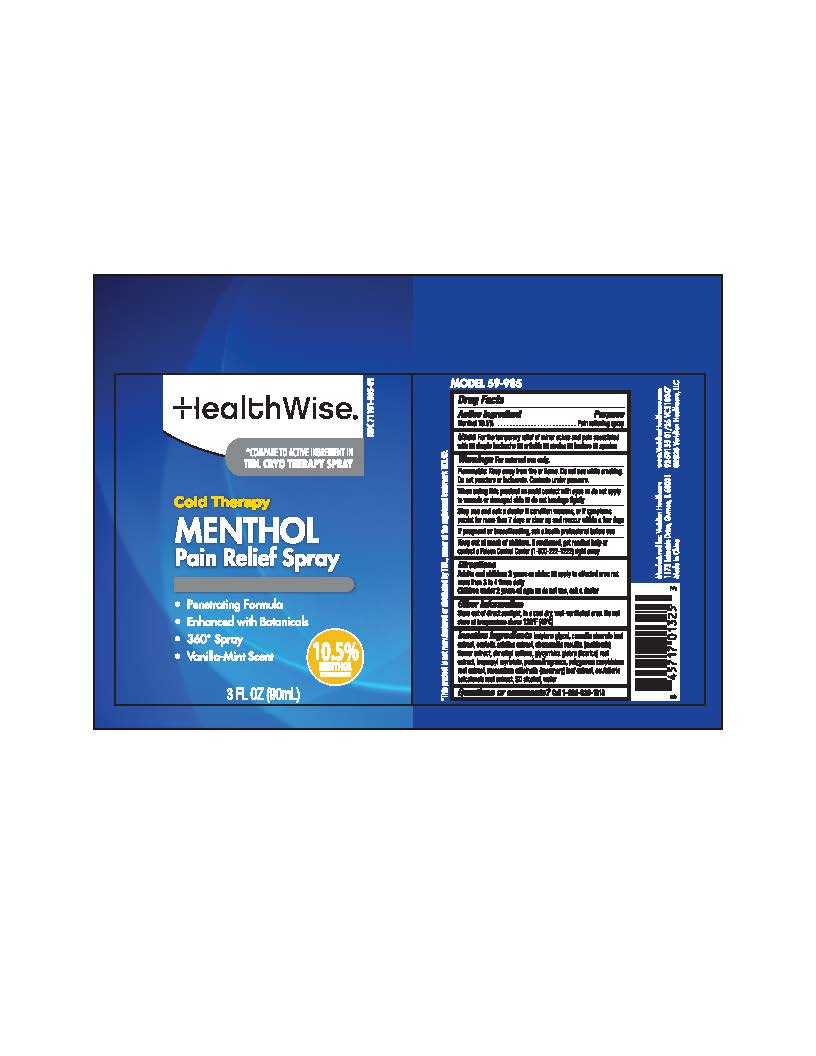 DRUG LABEL: HealthWise Cold Therapy Menthol Pain Relief
NDC: 71101-985 | Form: SPRAY
Manufacturer: Veridian Healthcare
Category: otc | Type: HUMAN OTC DRUG LABEL
Date: 20260113

ACTIVE INGREDIENTS: MENTHOL 10.5 mg/1 mL
INACTIVE INGREDIENTS: ALCOHOL; CHAMOMILE; DIMETHYL SULFONE; ISOPROPYL MYRISTATE; WATER; CAMELLIA SINENSIS LEAF; CENTELLA ASIATICA; POLYGONUM CUSPIDATUM ROOT; SCUTELLARIA BAICALENSIS ROOT; GLYCYRRHIZA GLABRA (LICORICE) ROOT; ROSMARINUS OFFICINALIS FLOWERING TOP; BUTYLENE GLYCOL

HealthWise Cold Theraphy Menthol Pain Relief Spray

Active ingredient

Menthol 10.5%

Purpose

Pain relieving spray

Uses

Uses For the temporary relief of minor pain associated with • arthritis • simple backache • strains • sprains • bruises

Warnings

For external use only.

Flammable.Do not use while smoking or near heat or flame. Donot use while smoking. Do not punture or incinirate. Contents under pressure.

When using this product

• avoid contact with eyes

• do not apply to wounds or damage skin

• do not bandage tightly

Stop use and ask a doctor if

- condition worsens, or if symptoms persist for more than 7 days or clear up and reoccur withing a few days

Keep out of reach of children.

If swallowed, get medical help or contact a Poison Control Center (1-800-222-1222) right away

Directions

- Adults and children 2 years or older:Apply to affected area not more than 3 to 4 times daily.

- Children under 2 years of age:do not use , ask a doctor.

Other information

Store out of direct sunlight, in a cool dry, well-ventilated area. Do not store at temperature above 120F (49C)

Inactive ingredients

butylene glycol, camellia sinensis leaf extract, centella asiatica extract, chamomilla recutita (matricaria) flower extract, dimethyl sulfone, glycyrrhiza glabra (licorice) root extract, isopropyl myristate, polygonum cuspidatum root extract, rosmarinus officinalis (rosemary) leaf extract, scutellaria baicalensis root extract, SD alcohol, water

Questions or comments?

1-888-326-1313